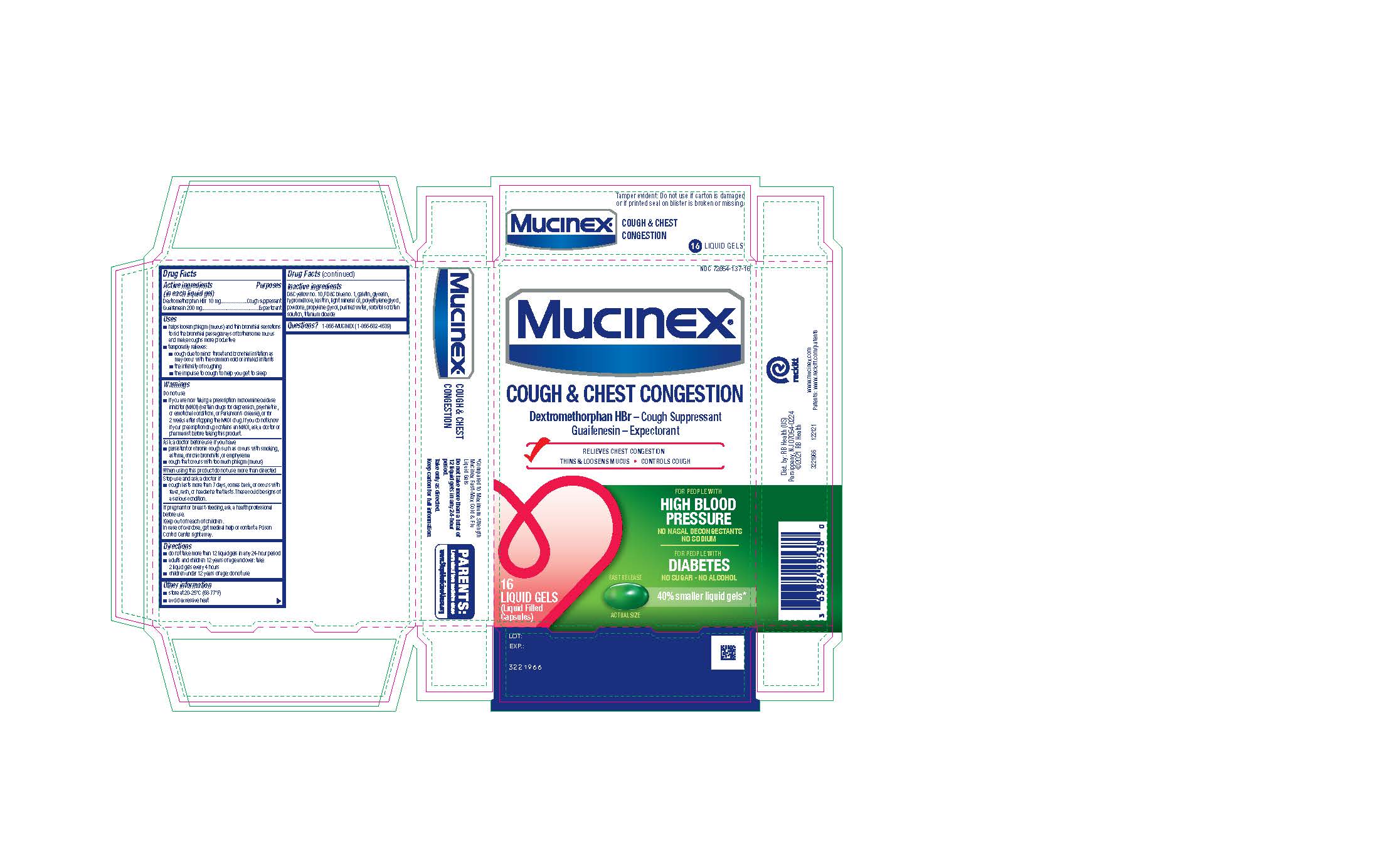 DRUG LABEL: Mucinex Cough Chest Congestion
NDC: 72854-137 | Form: CAPSULE, LIQUID FILLED
Manufacturer: RB Health (US) LLC
Category: otc | Type: HUMAN OTC DRUG LABEL
Date: 20241223

ACTIVE INGREDIENTS: DEXTROMETHORPHAN HYDROBROMIDE 10 mg/1 1; GUAIFENESIN 200 mg/1 1
INACTIVE INGREDIENTS: POLYETHYLENE GLYCOL, UNSPECIFIED; SORBITOL SOLUTION; TITANIUM DIOXIDE; FD&C BLUE NO. 1; HYPROMELLOSE, UNSPECIFIED; GLYCERIN; GELATIN, UNSPECIFIED; POVIDONE, UNSPECIFIED; D&C YELLOW NO. 10; LECITHIN, SOYBEAN; LIGHT MINERAL OIL; PROPYLENE GLYCOL; WATER

Mucinex® Cough & Chest Congestion

Drug Facts

ACTIVE INGREDIENT

Dextromethorphan HBr 10 mg.

Guaifenesin 200 mg

Uses

■ helps loosen phlegm (mucus) and thin bronchial secretions
to rid the bronchial passageways of bothersome mucus
and make coughs more productive
■ temporarily relieves:
■ cough due to minor throat and bronchial irritation as
may occur with the common cold or inhaled irritants
■ the intensity of coughing
■ the impulse to cough to help you get to sleep

Warnings

Do not use
■ if you are now taking a prescription monoamine oxidase
inhibitor (MAOI) (certain drugs for depression, psychiatric,
or emotional conditions, or Parkinson’s disease), or for
2 weeks after stopping the MAOI drug. If you do not know
if your prescription drug contains an MAOI, ask a doctor or
pharmacist before taking this product.

Directions

■ do not take more than 12 liquid gels in any 24-hour period
■ adults and children 12 years of age and over: take
2 liquid gels every 4 hours
■ children under 12 years of age: do not use

Other Information

■ store at 20-25°C (68-77°F)
■ avoid excessive heat

Inactive Ingredients

D&C yellow no. 10, FD&C blue no. 1, gelatin, glycerin,
hypromellose, lecithin, light mineral oil, polyethylene glycol,
povidone, propylene glycol, purified water, sorbitol sorbitan
solution, titanium dioxide

Questions?

1-866-MUCINEX (1-866-682-4639)

Dist. by: RB Health (US)
Parsippany, NJ 07054-0224
©2021 RB Health

Keep out of reach of children

Principal Display Panel

Fast Dissolving Liquid Gels!

NDC 72854-137-16

Mucinex®

Cough & Chest Congestion

Dextromethorphan HBr – Cough Suppressant
Guaifenesin – Expectorant

✓Thins & Loosens Mucus
✓Relieves Chest Congestion
✓Controls Cough

16
LIQUID GELS
(Liquid Filled Capsules)

Actual Size

FOR AGES 12+